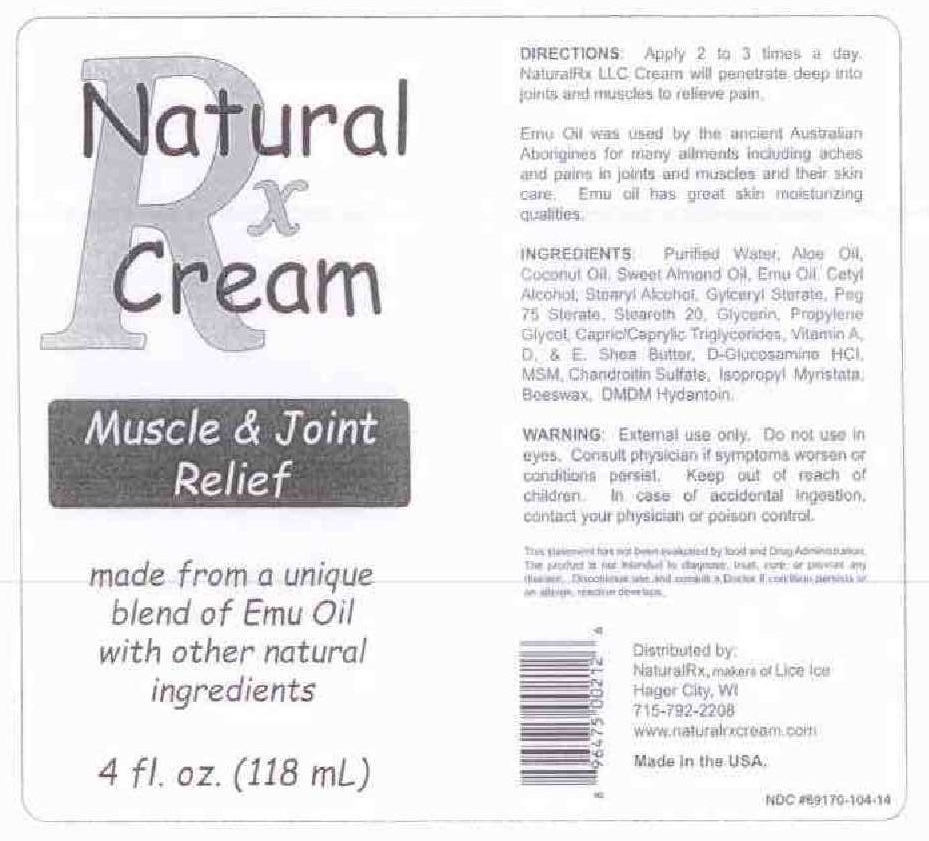 DRUG LABEL: MUSCLE AND JOINT RELIEF
NDC: 69170-104 | Form: CREAM
Manufacturer: NATURALRX LLC
Category: homeopathic | Type: HUMAN OTC DRUG LABEL
Date: 20200322

ACTIVE INGREDIENTS: EMU OIL 1 [hp_X]/100 mL
INACTIVE INGREDIENTS: WATER; ALOE VERA LEAF; COCONUT OIL; ALMOND OIL; CETYL ALCOHOL; STEARYL ALCOHOL; GLYCERYL MONOSTEARATE; PEG-75 STEARATE; STEARETH-20; GLYCERIN; PROPYLENE GLYCOL; MEDIUM-CHAIN TRIGLYCERIDES; VITAMIN A PALMITATE; CHOLECALCIFEROL; .ALPHA.-TOCOPHEROL ACETATE; SHEA BUTTER; GLUCOSAMINE HYDROCHLORIDE; DIMETHYL SULFONE; CHONDROITIN SULFATE (CHICKEN); ISOPROPYL MYRISTATE; YELLOW WAX; DMDM HYDANTOIN

ACTIVE INGREDIENTS

EMU OIL.....1 X

PURPOSE

PAIN RELIEF

WARNINGS

FOR EXTERNAL USE ONLY.

DO NOT USE IN EYES.

CONSULT PHYSICIAN IF SYMPTOMS WORSEN OR CONDITIONS PERSISTS.

KEEP OUT OF REACH OF CHILDREN. IN CASE OF ACCIDENTAL INGESTION, CONSULT YOUR PHYSICIAN OR POISON CONTROL.

USES

NATURAL RX LLC CREAM WILL PENETRATE DEEP INTO JOINTS AND MUSCLES TO RELIEVE PAIN.

DIRECTIONS

APPLY 2 TO 3 TIMES A DAY.

INGREDIENTS:

PURIFIED WATER, ALOE OIL, COCONUT OIL, SWEET ALMOND OIL, CETYL ALCOHOL, STEARYL ALCOHOL, GLYCERYL STEARATE, PEG-75 STEARATE, STEARETH 20, GLYCERIN, PROPYLENE GLYCOL, CAPRYLIC/CAPRIC TRIGLYCERIDES, VITAMIN A, D & E, SHEA BUTTER, D-GLUCOSAMINE HCL, MSM, CHONDROITIN SULFATE, ISOPROPYL MYRISTATE, BEESWAX, DMDM HYDANTOIN.